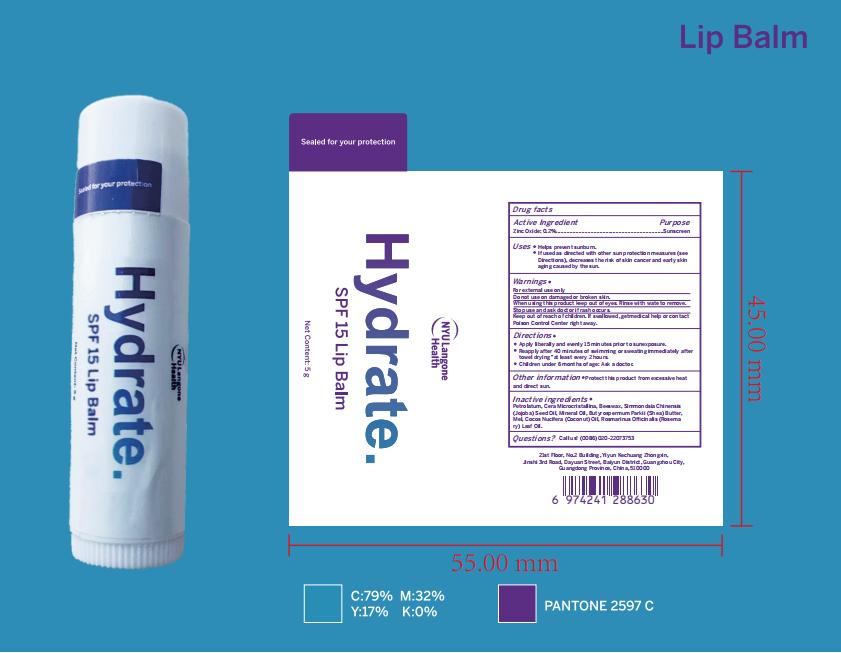 DRUG LABEL: NYU Langone Health Lip Balm
NDC: 74458-045 | Form: LIPSTICK
Manufacturer: Guangzhou Yilong Cosmetics Co., Ltd
Category: otc | Type: HUMAN OTC DRUG LABEL
Date: 20250625

ACTIVE INGREDIENTS: ZINC OXIDE 0.2 g/100 g
INACTIVE INGREDIENTS: MINERAL OIL; JOJOBA OIL; SHEA BUTTER; YELLOW WAX

NYU Langone Health Lip Balm

Active ingredients

Zinc Oxide 0.2%

Purpose

Sunscreen

Uses

Helps prevent sunburn.
If used as directed with other sun protection measures (see Directions), decreases the risk of skin cancer and early skin aging caused by the sun.

Warnings

For external use only.

Stop use and ask doctor if rash occurs.

Do not use on damaged or broken skin.

When using this product keep out of eyes. Rinse with wate to remove.

Keep out of reach of children. lf swallowed, getmedical help or contact
Poison Control Center right away.

Dosage

Squeeze out an appropriate amount of Sunscreen lip balm and spread evenly on your lips.

Inactive ingredients

PETROLATUM：69%
CERA MICROCRISTALLINA：13%
BEESWAX：5%
SIMMONDSIA CHINENSIS (JOJOBA) SEED OIL：5%
MINERAL OIL：4.4%
BUTYROSPERMUM PARKII(SHEA) BUTTER：2%
MEL：1%
COCOS NUCIFERA (COCONUT) OIL：0.2%
ROSMARINUS OFFICINALIS (ROSEMARY) LEAF OIL：0.2%